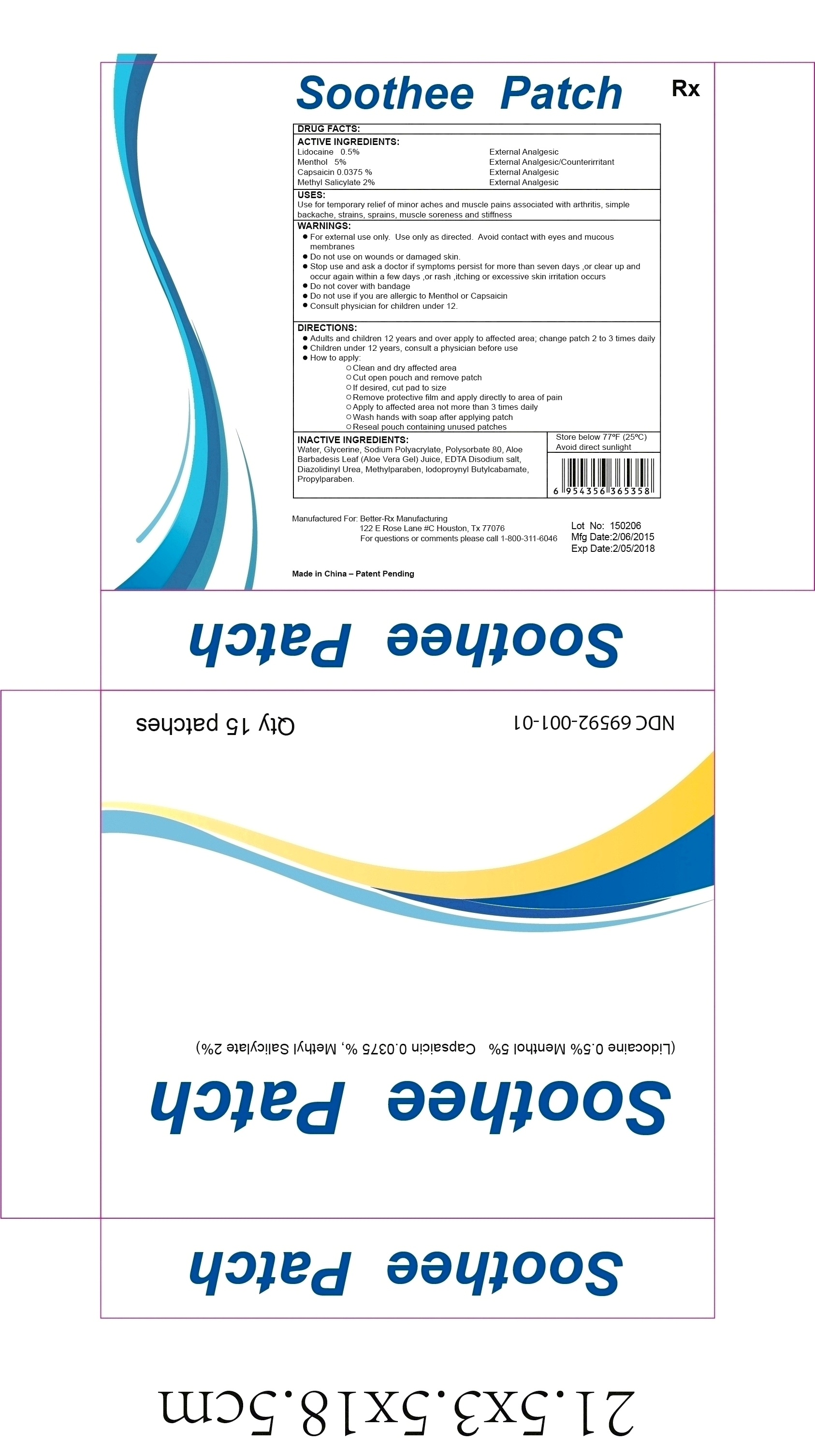 DRUG LABEL: Soothee Patch
                
                
NDC: 69592-001 | Form: PATCH
Manufacturer: Better Pain Solutions, LLC 
Category: prescription | Type: HUMAN PRESCRIPTION DRUG LABEL
Date: 20150319

ACTIVE INGREDIENTS: LIDOCAINE 0.5 mg/10 g; MENTHOL 5 mg/10 g; CAPSAICIN 0.0375 g/10 g; METHYL SALICYLATE 2 g/10 g
INACTIVE INGREDIENTS: WATER; GLYCERIN; SODIUM POLYACRYLATE (2500000 MW); POLYSORBATE 80; ALOE VERA LEAF; EDETATE DISODIUM; DIAZOLIDINYL UREA; METHYLPARABEN; IODOPROPYNYL BUTYLCARBAMATE; PROPYLPARABEN

Drug Facts

DESCRIPTION

ACTIVE INGREDIENTS:

Lidocaine 0.5% External Analgesic

Menthol 5% External Analgesic/Counterirritant

Capsaicin 0.0375% External Analgesic

Methyl Salicylate 2% External Analgesic

USES:

Use for temporary relief of minor aches and muscle pains associated with arthritis, simple

backache, strains, sprains, muscle soreness and stiffness

WARNINGS:

- For external use only. Use only as directed. Avoid contact with eyes and mucus membranes
- Do not use on wounds or damaged skin
- Stop use and ask a doctor if symptoms persist for more than seven days or clear up and occur again within a few days, or rahs, itching or excessive skin irritation occurs
- Do not cover with bandage
- Do no use if you are allergic to Menthol or Capsaicin
- Consult physician for children under 12

DIRECTIONS:

- Adults and children 12 years and over apply to affected area; change patch 2 to 3 times daily
- Children under 12 years, consult a physician before use
- How to apply:

- Clean and dry affected area
- Cut open pouch and remove patch
- If desired, cut patch to size
- Remove protective film and apply directly to area of pain
- Apply to affected area not more than 3 times daily
- Wash hands with soap after applying patch
- Reseal pouch containing unused patches

INACTIVE INGREDIENTS:

Water, Glycerine, Sodium Polyacrylate, Polysorbate 80, Aloe

Barbadensis Leaf (Aloe Vera Gel) Juice, EDTA Disodium salt,

Diazolidinyl Urea, Methylparaben, Iodopropynyl Butylcabamate,

Propylparaben

STORAGE AND HANDLING

Store below 77F (25C)

Avoid direct sunlight

PATIENT INFORMATION

Soothee Patch

Better-Rx Manufacturing

The potential exists for a small child or pet to suffer serious

effect from chewing or ingesting a new or used Soothee Patch,

although the risk with this formulation has not been evaluated.

It is important for pateints to store and dispose of Soothee

Patch out of the reach of children, pets and others. (See

HANDLING AND DISPOSAL)

Excessive Dosing

Excessive Dosing by applying Soothee Patch to larger areas for

longer than recommmended wearing time could result in increased absorption and higher blood concentrations. Longer

duration of application, application of more than the

recommended number of patches, smaller patients,

or impaired elimination may all contribute to increasing the blood concentration.

PRECAUTIONS

General

Allergic Reactions

Patients allergic to menthol or capsaicin or any other

ingredient in Soothee Patch should not use the Soothee Patch.

Non-intact Skin

Application tobroken or inflamed skin, although not tested,

may result in higher blood concentrations from increased absorption.

Eye Exposure

The contact of Soothee Patch with eyes, altough not studied, should be avoided

based on the findings of sever eye irritations with the use of similar products in animals.

If eye contact occurs, immediately wash out the eye with water or saline.

Pregnancy

Nursing Mothers

Soothee Patch has not been studied in nursing mothers.

Caution should be exercised when administering the Soothee

Patch to nursing mothers. When soothee patch is used concurrently with other products in the same class

Pediatric Use

Soothee Patch Safety and effectiveness has not been established in pediatric patients.

DOSAGE AND ADMINISTRATION

Apply Soothee Patch to intact skin to cover the area most

sensitive to pain. Apply up to four (4) patches per day. Each

patch should not be applied for more than 8 hours in a given

24-hour period. Patches may be cut into smaller sizes with scissors

prior to removal of the release liner. Clothing may be worn over the area of application.

Smaller areas of treatment are recommended in a debilitated patient, or patient with impaired elimination.

If irritation or a burning sensation occurs during application,

remove the patch and do not reapply until the irritation subsides. When Soothee Patch is used

concomitantly with other products containing same or similar agents, the amount

absorbed from all formulations must be considered.

HANDLING AND DISPOSAL

Hands should be washed after handling Soothee Patch, and eye contact

with Soothee Patch should be avoided. Do not store patch outside the sealed envelope.

Apply immediately after removal from the protective envelope. Fold use patches so that the adhesive

side sticks to itself and safely discard used patches or pieces of cut patches where children and pets

cannot get to them. Soothee Patch should be kept out of reach of children.

HOW SUPPLIED

Soothee Patch (Lidocaine 0.5%/Menthol 5%/Capsaicin

0.0375%/Methyl Salicylate 2%) is available as the following:

Box of 15 patches, packaged into 3 child-resistant envelopes (5

patches /envelope)

Patient Information

Soothee Patch is dispensed by prescription (Rx) under medical supervision and direction

Product Code: 69592-001-01

Better-Rx Manufacturing does not represent this product code to be a National Drug Codes

(NDC). Product Codes are formatted according to standard industry practice, to meet the

formatting requirements of pharmacy and health insurance computer systems.

Store below 77F (25C); excursion permitted to 59-85F (15-30C) See USP Controlled Room Temperature.

Manufactured for:

Better-Rx Manufacturing

122 E Rose Lane No.C Houston Tx 77076

For questions or comments please call 1-800-311-6046

March 2015